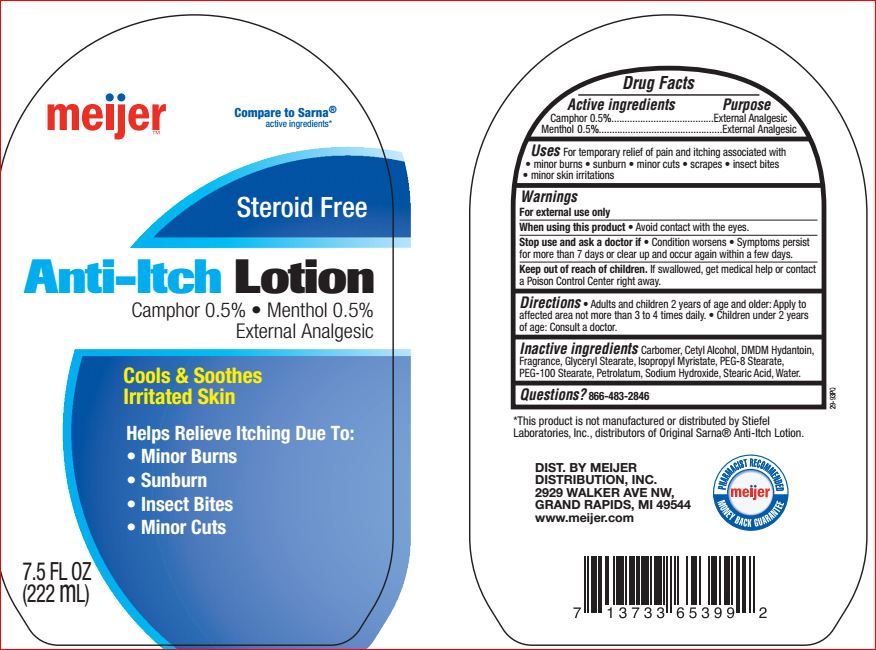 DRUG LABEL: Anti-Itch
NDC: 41250-797 | Form: LOTION
Manufacturer: Meijer
Category: otc | Type: HUMAN OTC DRUG LABEL
Date: 20180621

ACTIVE INGREDIENTS: CAMPHOR (SYNTHETIC) 0.5 g/100 mL; Menthol 0.5 g/100 mL
INACTIVE INGREDIENTS: CARBOMER HOMOPOLYMER TYPE C (ALLYL PENTAERYTHRITOL CROSSLINKED); Cetyl Alcohol; DMDM Hydantoin; GLYCERYL MONOSTEARATE; Isopropyl Myristate; PEG-8 Stearate; PEG-100 Stearate; Petrolatum; Sodium Hydroxide; Stearic Acid; WATER

Drug Facts

Active ingredients Purpose
Camphor 0.5%.......................................External Analgesic
Menthol 0.5%.........................................External Analgesic

Uses

For temporary relief of pain and itching associated with
• minor burns • sunburn • minor cuts • scrapes • insect bites
• minor skin irritations

Warnings
For external use only
When using this product • Avoid contact with the eyes.
Stop use and ask a doctor if • Condition worsens • Symptoms persist
for more than 7 days or clear up and occur again within a few days.
Keep out of reach of children. If swallowed, get medical help or contact
a Poison Control Center right away

DOSAGE AND ADMINISTRATION

Directions • Adults and children 2 years of age and older: Apply to
affected area not more than 3 to 4 times daily. • Children under 2 years
of age: Consult a doctor.

Inactive ingredients

Carbomer
Cetyl Alcohol
DMDM Hydantoin
Fragrance
Glyceryl Stearate
Isopropyl Myristate
PEG-8 Stearate
PEG-100 Stearate
Petrolatum
Sodium Hydroxide
Stearic Acid
Water